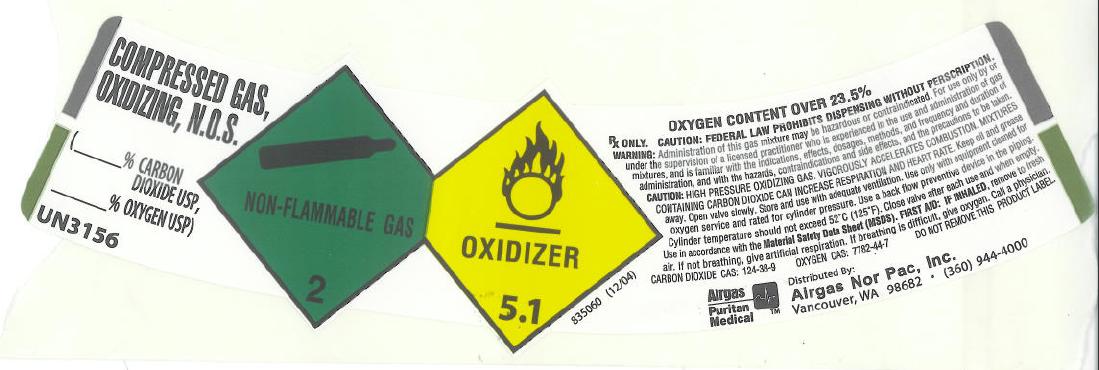 DRUG LABEL: Carbon Dioxide Oxygen Mix
NDC: 57472-005 | Form: GAS
Manufacturer: AIRGAS-NORPAC INC.
Category: prescription | Type: HUMAN PRESCRIPTION DRUG LABEL
Date: 20111229

ACTIVE INGREDIENTS: Carbon Dioxide 200 mL/1 L; Oxygen 800 mL/1 L

Carbon Dioxide Oxygen Mix

PACKAGE LABEL

COMPRESSED GAS, OXIDIZING, N.O.S.

% CARBON DIOXID USP

% OXYGEN USP

UN3156

NON-FLAMMABLE GAS 2

OXIDIZER 5.1

Rx ONLY. CAUTION FEDERAL LAW PROHIBITS DISPENSING WITHOUT PRESCRIPTION. WARNING: Administration of this gas mixture may be hazardous or contraindicated. For use only by or under the supervision of a licensed practitioner who is experienced in the use and administration of gas mixtures, and is familiar with the indications, effects, dosage, methods, and frequency and duration of administration, and with the hazards, contraindications and side effects, and the precautions to be taken.

CAUTION: HIGH PRESSURE OXIDIZING GAS. VIGOROUSLY ACCELERATES COMBUSTION. MIXTURES CONTAINING CARBON DIOXIDE CAN INCREASE RESPIRATION AND HEART RATE. Keep oil and grease away. Open valve slowly. Store and use with adequate ventilation. Use only with equipment cleaned for oxygen service and rated for cylinder pressure. Use a back flow preventive device in the piping. Cylinder temperature should not exceed 52 degrees C (125 degrees F). Close valve after each use and when empty. Use in accordance with Material Safety Data Sheet (MSDS). FIRST AID: IF INHALED, remove to fresh air. If not breathing, give artificial respiration. If breathing is difficult, give oxygen. Call a physician. CARBON DIOXIDE CAS: 124-28-9 OXYGEN CAS: 7782-44-7 DO NOT REMOVE THIS PRODUCT LABEL.

Airgas Puritan Medical

Distributed By:

Airgas Nor Pac, Inc.

Vancouver, WA 98682

(360) 949-4000